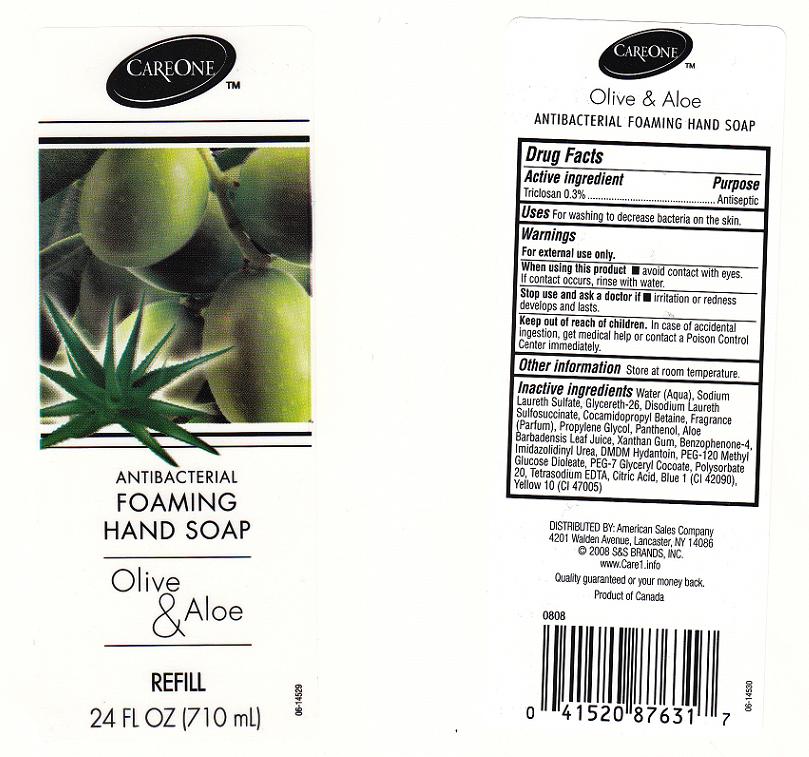 DRUG LABEL: ANTIBACTERIAL FOAMING   
NDC: 41520-170 | Form: LIQUID
Manufacturer: AMERICAN SALES COMPANY
Category: otc | Type: HUMAN OTC DRUG LABEL
Date: 20111025

ACTIVE INGREDIENTS: TRICLOSAN 0.3 mL/100 mL
INACTIVE INGREDIENTS: WATER; SODIUM LAURETH SULFATE; GLYCERETH-26; DISODIUM LAURETH SULFOSUCCINATE; COCAMIDOPROPYL BETAINE; PROPYLENE GLYCOL; PANTHENOL; ALOE VERA LEAF; XANTHAN GUM; SULISOBENZONE; IMIDUREA; DMDM HYDANTOIN; PEG-120 METHYL GLUCOSE DIOLEATE; PEG-7 GLYCERYL COCOATE; POLYSORBATE 20; EDETATE SODIUM; ANHYDROUS CITRIC ACID; FD&C BLUE NO. 1; D&C YELLOW NO. 10

DRUG FACTS

ACTIVE INGREDIENT

TRICLOSAN 0.3 PERCENT

PURPOSE

ANTISEPTIC

USES

FOR WASHING TO DECREASE BACTERIA ON THE SKIN.

WARNINGS

FOR EXTERNAL USE ONLY.

WHEN USING THIS PRODUCT

AVOID CONTACT WITH EYES. IF CONTACT OCCURS, RINSE WITH WATER.

STOP USING THIS PRODUCT AND ASK DOCTOR IF

IRRITATION OR REDNESS DEVELOPS AND LASTS.

KEEP OUT OF REACH OF CHILDREN

IN CASE OF ACCIDENTAL INGESTION, GET MEDICAL HELP OR CONTACT A POISON CONTROL CENTER IMMEDIATELY.

DIRECTIONS

APPLY ONTO WET HANDS AND WORK INTO A LATHER. RINSE THOROUGHLY.

OTHER INFORMATION

STORE AT ROOM TEMPERATURE.

INACTIVE INGREDIENTS

WATER, SODIUM LAURETH SULFATE, GLYCERETH-26, DISODIUM LAURETH SULFOSUCCINATE, COCAMIDOPROPYL BETAINE, FRAGRANCE, PROPYLENE GLYCOL, PANTHENOL, ALOE BARBADENSIS LEAF JUICE, XANTHAN GUM, BENZOPHENONE-4, IMIDAZOLIDYNL UREA, DMDM HYDANTOI N, PEG-120 METHYL GLUCOSE DIOLEATE, PEG-7 GLYCERYL COCOATE, POLYSORBATE 20, TETRASODIUM EDTA, CITRIC ACID, BLUE 1 (CI 42090), YELLOW 10 (CI 47005).